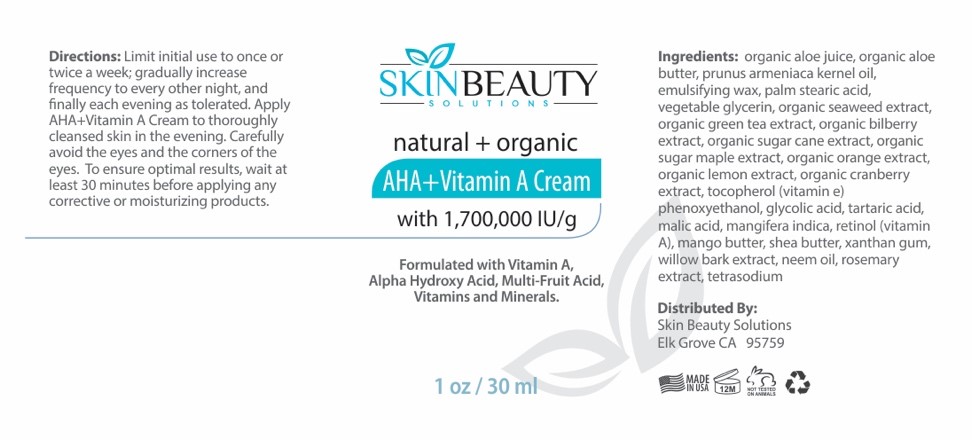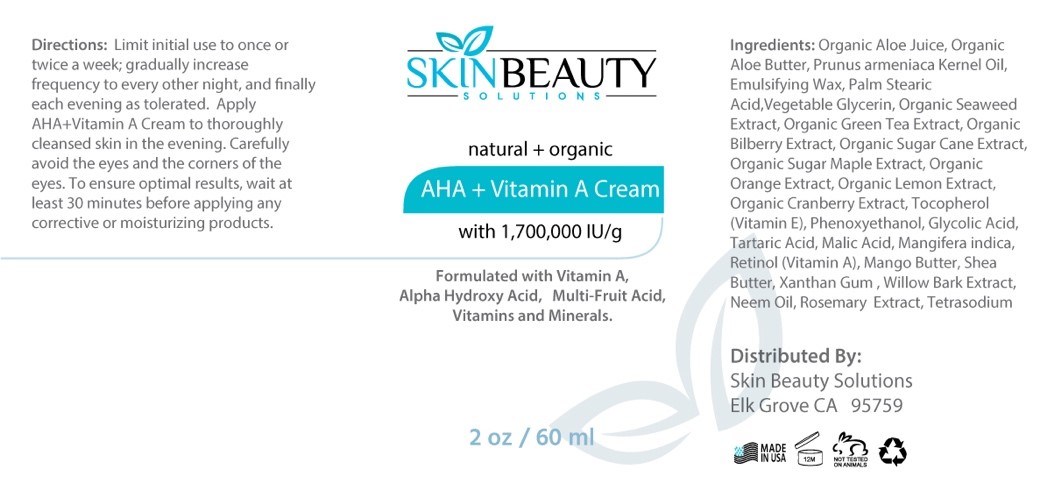 DRUG LABEL: Retinol plus AHA Cream
NDC: 84785-0008 | Form: SOLUTION
Manufacturer: Gazebo Wellness SKIN LLC
Category: otc | Type: HUMAN OTC DRUG LABEL
Date: 20241216

ACTIVE INGREDIENTS: CRANBERRY SEED 0.3 mg/30 mL; WILLOW BARK 0.3 mg/30 mL; GREEN TEA LEAF 0.3 mg/30 mL; MANGO 0.3 mg/30 mL; SHEA BUTTER 0.3 mg/30 mL; ROSEMARY 0.3 mg/30 mL; APRICOT KERNEL OIL 0.3 mg/30 mL; GLYCOLIC ACID 0.3 mg/30 mL; ORANGE JUICE 0.3 mg/30 mL; LEMON 0.3 mg/30 mL; MALIC ACID 0.3 mg/30 mL; TARTARIC ACID 0.3 mg/30 mL; RETINOL 0.3 mg/30 mL; BILBERRY JUICE 0.3 mg/30 mL; ALOE VERA LEAF 0.3 mg/30 mL
INACTIVE INGREDIENTS: STEARIC ACID; PHENOXYETHANOL; VITAMIN E POLYETHYLENE GLYCOL SUCCINATE; XANTHAN GUM; TETRASODIUM EDETATE DIHYDRATE; GLYCERIN

DOSAGE AND ADMINISTRATION

SKINBEAUTY
SOLUTIONS
natural + organic AHA+Vitamin A Cream
with 1,700,000 IU/g
Formulated with Vitamin A, Alpha Hydroxy Acid, Multi-Fruit Acid, Vitamins and Minerals.

WARNINGS

Limit initial use to once or twice a week; gradually increase frequency to every other night, and finally each evening as tolerated. Apply AHA+Vitamin A Cream to thoroughly cleansed skin in the evening. Carefully avoid the eyes and the corners of the eyes. To ensure optimal results, wait at least 30 minutes before applying any corrective or moisturizing products.

INACTIVE INGREDIENT

Inactive ingredients: Emulsifying Wax, Palm Stearic Acid, Vegetable Glycerin, Phenoxyethanol, Xanthan Gum, Tetrasodium EDTA.

INDICATIONS AND USAGE

Directions: Limit initial use to once or twice a week; gradually increase frequency to every other night, and finally each evening as tolerated. Apply AHA+Vitamin A Cream to thoroughly cleansed skin in the evening. Carefully avoid the eyes and the corners of the eyes. To ensure optimal results, wait at least 30 minutes before applying any corrective or moisturizing products.

keep out of reach of children

PURPOSE

natural + organic AHA+Vitamin A Cream
with 1,700,000 IU/g
Formulated with Vitamin A, Alpha Hydroxy Acid, Multi-Fruit Acid, Vitamins and Minerals.
Distributed By:
Skin Beauty Solutions Elk Grove CA 95759

ACTIVE INGREDIENT

Active ingredients: Organic Aloe Juice, Organic Aloe Butter, Apricot Kernel Oil, Organic Seaweed Extract, Organic Green Tea Extract, Organic Bilberry Extract, Organic Sugar Cane Extract, Organic Sugar Maple Extract, Organic Orange Extract, Organic Lemon Extract, Organic Cranberry Extract, Vitamin E, Glycolic Acid, Tartaric Acid, Malic Acid, Mango, Retinol, Mango Butter, Shea Butter, Willow Bark Extract, Neem Oil, Rosemary Extract.

PACKAGE LABEL

Content of labeling